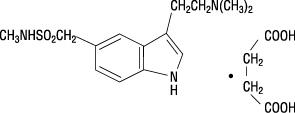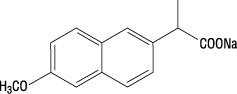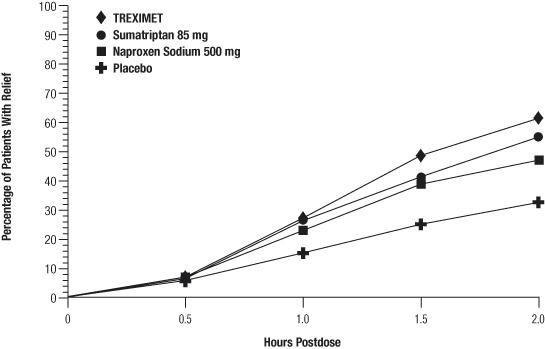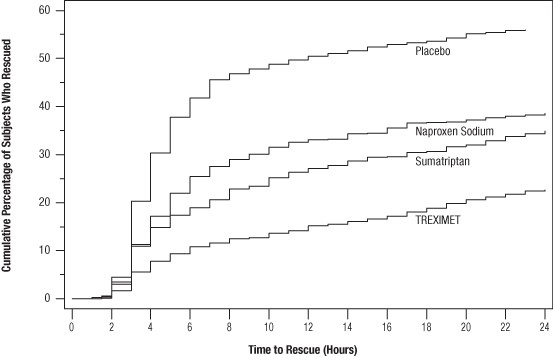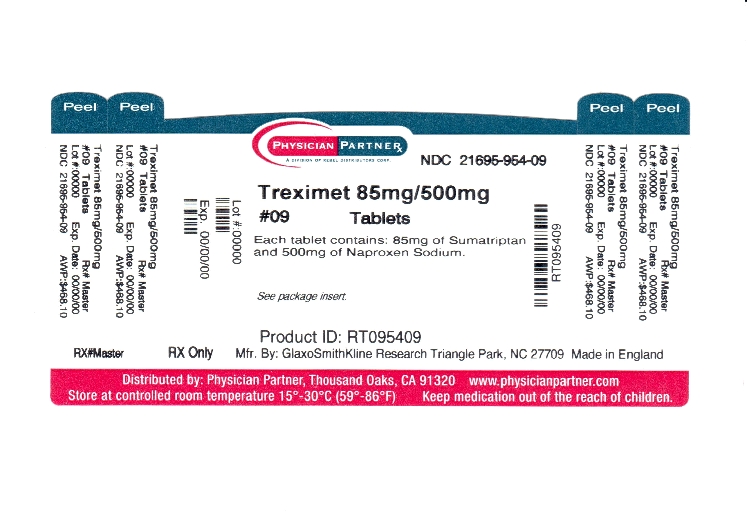 DRUG LABEL: TREXIMET
NDC: 21695-954 | Form: TABLET, FILM COATED
Manufacturer: Rebel Distributors Corp
Category: prescription | Type: HUMAN PRESCRIPTION DRUG LABEL
Date: 20110913

ACTIVE INGREDIENTS: SUMATRIPTAN SUCCINATE 85 mg/1 1; NAPROXEN SODIUM 500 mg/1 1
INACTIVE INGREDIENTS: CROSCARMELLOSE SODIUM; DEXTROSE MONOHYDRATE; ANHYDROUS DIBASIC CALCIUM PHOSPHATE; FD&C BLUE NO. 2; LECITHIN, SOYBEAN; MAGNESIUM STEARATE; MALTODEXTRIN; CELLULOSE, MICROCRYSTALLINE; POVIDONE; SODIUM BICARBONATE; CARBOXYMETHYLCELLULOSE SODIUM; TALC; TITANIUM DIOXIDE

TREXIMET®
(sumatriptan and naproxen sodium)
Tablets

WARNINGS

Cardiovascular Risk: TREXIMET may cause an increased risk of serious cardiovascular thrombotic events, myocardial infarction, and stroke, which can be fatal. This risk may increase with duration of use. Patients with cardiovascular disease or risk factors for cardiovascular disease may be at greater risk (see WARNINGS: Cardiovascular Effects).

Gastrointestinal Risk: TREXIMET contains a nonsteroidal anti-inflammatory drug (NSAID). NSAID-containing products cause an increased risk of serious gastrointestinal adverse events including bleeding, ulceration, and perforation of the stomach or intestines, which can be fatal. These events can occur at any time during use and without warning symptoms. Elderly patients are at greater risk for serious gastrointestinal events (see WARNINGS: Risk of Gastrointestinal Ulceration, Bleeding, and Perforation With Nonsteroidal Anti-inflammatory Drug Therapy).

DESCRIPTION

TREXIMET contains sumatriptan (as the succinate), a selective 5-hydroxytryptamine1 (5-HT1) receptor subtype agonist, and naproxen sodium, a member of the arylacetic acid group of nonsteroidal anti-inflammatory drugs (NSAIDs).

Sumatriptan succinate is chemically designated as 3-[2-(dimethylamino)ethyl]-N-methyl-indole-5-methanesulfonamide succinate (1:1), and it has the following structure:

The empirical formula is C14H21N3O2S•C4H6O4, representing a molecular weight of 413.5. Sumatriptan succinate is a white to off-white powder that is readily soluble in water and in saline.

Naproxen sodium is chemically designated as (S)-6-methoxy-α-methyl-2-naphthaleneacetic acid, sodium salt, and it has the following structure:

The empirical formula is C14H13NaO3, representing a molecular weight of 252.23. Naproxen sodium is a white-to-creamy white crystalline solid, freely soluble in water at neutral pH.

Each TREXIMET Tablet for oral administration contains 119 mg of sumatriptan succinate equivalent to 85 mg of sumatriptan and 500 mg of naproxen sodium. Each tablet also contains the inactive ingredients croscarmellose sodium, dextrose monohydrate, dibasic calcium phosphate, FD&C Blue No. 2, lecithin, magnesium stearate, maltodextrin, microcrystalline cellulose, povidone, sodium bicarbonate, sodium carboxymethylcellulose, talc, and titanium dioxide.

CLINICAL PHARMACOLOGY

Mechanism of Action

TREXIMET contains sumatriptan, a 5-HT1 receptor agonist that mediates vasoconstriction of the human basilar artery and vasculature of human dura mater, which correlates with the relief of migraine headache. It also contains naproxen, an NSAID that inhibits the synthesis of inflammatory mediators. Therefore, sumatriptan and naproxen contribute to the relief of migraine through pharmacologically different mechanisms of action.

Sumatriptan is a 5-HT1 receptor agonist that binds with high affinity to 5-HT1B and 5-HT1D receptors. Sumatriptan has only a weak affinity for 5-HT1A, 5-HT5A, and 5-HT7 receptors and no significant affinity (as measured using standard radioligand binding assays) or pharmacological activity at 5-HT2, 5-HT3, or 5-HT4 receptor subtypes or at alpha1-, alpha2-, or beta-adrenergic; dopamine1; dopamine2; muscarinic; or benzodiazepine receptors. In addition to causing vasoconstriction, experimental data from animal studies show that sumatriptan also activates 5-HT1 receptors on peripheral terminals of the trigeminal nerve innervating cranial blood vessels. Such an action may contribute to the antimigrainous effect of sumatriptan in humans. In the anesthetized dog, sumatriptan selectively reduces carotid arterial blood flow with little or no effect on arterial blood pressure or total peripheral resistance.

Naproxen sodium is an NSAID with analgesic and antipyretic properties. The sodium salt of naproxen has been developed as a more rapidly absorbed formulation of naproxen for use as an analgesic. The mechanism of action of the naproxen anion, like that of other NSAIDs, is not completely understood but may be related to prostaglandin synthetase inhibition.

Pharmacokinetics

TREXIMET is a formulation of 85 mg of sumatriptan (as sumatriptan succinate) and 500 mg of naproxen sodium with a distinct pharmacokinetic profile. Cmax (median, range) for sumatriptan following administration of TREXIMET occurs at approximately 1 hour (0.3 to 4.0 hours). Cmax (median, range) for naproxen following administration of TREXIMET occurs at approximately 5 hours (0.3 to 12 hours). The sumatriptan half-life is approximately 2 hours (15% to 43% CV) and the naproxen half-life is approximately 19 hours (13% to 15% CV). The mean Cmax for sumatriptan when given as TREXIMET is similar to that of sumatriptan when given as IMITREX® (sumatriptan succinate) Tablets 100 mg alone. The median sumatriptan Tmax is only slightly different (1 hour for TREXIMET and 1.5 hours for IMITREX). The Cmax for naproxen is approximately 36% lower, and the Tmax occurs approximately 4 hours later from TREXIMET than from ANAPROX® DS (naproxen sodium tablets) 550 mg. AUC values for sumatriptan and for naproxen are similar for TREXIMET compared to IMITREX or ANAPROX DS, respectively. In a crossover study in 16 patients, the pharmacokinetics of both components administered as TREXIMET were similar during a migraine attack and during a migraine-free period.

Absorption and Bioavailability: Bioavailability of sumatriptan is approximately 15%, primarily due to presystemic (first-pass) metabolism and partly due to incomplete absorption.

Naproxen is rapidly and completely absorbed from the gastrointestinal tract with an in vivo bioavailability of 95%.

Food Effects: Food had no significant effect on the bioavailability of sumatriptan or naproxen administered as TREXIMET, but slightly delayed the Tmax of sumatriptan by about 0.6 hour. These data indicate that TREXIMET may be administered without regard to food.

Distribution: The volume of distribution of sumatriptan is 2.4 L/kg. Plasma protein binding is 14% to 21%. The effect of sumatriptan on the protein binding of other drugs has not been evaluated, but would be expected to be minor, given the low protein binding.

The volume of distribution of naproxen is 0.16 L/kg. At therapeutic levels naproxen is greater than 99% albumin bound. At doses of naproxen greater than 500 mg/day, there is a less than proportional increase in plasma levels due to an increase in clearance caused by saturation of plasma protein binding at higher doses (average trough Css = 36.5, 49.2, and 56.4 mg/L with 500, 1,000, and 1,500 mg daily doses of naproxen, respectively). However, the concentration of unbound naproxen continues to increase proportionally to dose.

Metabolism: Most of a radiolabeled dose of sumatriptan excreted in the urine is the major metabolite indole acetic acid (IAA) or the IAA glucuronide, both of which are inactive. Three percent of the dose can be recovered as unchanged sumatriptan. In vitro studies with human microsomes suggest that sumatriptan is metabolized by monoamine oxidase (MAO), predominantly the A isoenzyme, and inhibitors of that enzyme may alter sumatriptan pharmacokinetics to increase systemic exposure (see CONTRAINDICATIONS and PRECAUTIONS: Drug Interactions: Monoamine Oxidase-A Inhibitors). No significant effect was seen with an MAO-B inhibitor.

Naproxen is extensively metabolized to 6-0-desmethyl naproxen, and both parent and metabolites do not induce metabolizing enzymes.

Elimination: Radiolabeled ^14C-sumatriptan administered orally is largely renally excreted (about 60%), with about 40% found in the feces. The elimination half-life of sumatriptan is approximately 2 hours.

The clearance of naproxen is 0.13 mL/min/kg. Approximately 95% of the naproxen from any dose is excreted in the urine, primarily as naproxen (less than 1%), 6-0-desmethyl naproxen (less than 1%), or their conjugates (66% to 92%). The plasma half-life of the naproxen anion in humans is approximately 19 hours. The corresponding half-lives of both metabolites and conjugates of naproxen are shorter than 12 hours, and their rates of excretion have been found to coincide closely with the rate of naproxen disappearance from the plasma. In patients with renal failure, metabolites may accumulate (see PRECAUTIONS: Renal Effects).

Special Populations

Renal Impairment: TREXIMET is not recommended for use in patients with creatinine clearance less than 30 mL/min (see PRECAUTIONS: Renal Effects). The effect of renal impairment on the pharmacokinetics of TREXIMET has not been studied.

Minimal change in clinical effect would be expected with regard to sumatriptan as it is largely metabolized to an inactive substance.

Since naproxen and its metabolites and conjugates are primarily excreted by the kidney, the potential exists for naproxen metabolites to accumulate in the presence of renal insufficiency. Elimination of naproxen is decreased in patients with severe renal impairment.

Hepatic Impairment: Because TREXIMET is a fixed-dose combination that cannot be adjusted for this patient population, it is contraindicated in patients with hepatic impairment (see CONTRAINDICATIONS and PRECAUTIONS: Hepatic Effects). The effect of hepatic impairment on the pharmacokinetics of TREXIMET has not been studied. Sumatriptan is contraindicated in patients with severe hepatic impairment and the dose is limited to 50 mg in patients with liver disease.

Age: The effect of age (elderly or pediatric patients) on the pharmacokinetics of TREXIMET has not been studied. Elderly patients are more likely to have decreased hepatic function and decreased renal function (see PRECAUTIONS: Geriatric Use).

The pharmacokinetics of oral sumatriptan in the elderly (mean age: 72 years, 2 males and 4 females) and in patients with migraine (mean age: 38 years, 25 males and 155 females) were similar to that in healthy male subjects (mean age: 30 years).

Gender: In a pooled analysis of 5 pharmacokinetic studies, there was no effect of gender on the systemic exposure of TREXIMET. In a study comparing the pharmacokinetics of sumatriptan in females and males, no differences were observed between genders for AUC, Cmax, Tmax, and T½.

Race: The effect of race on the pharmacokinetics of TREXIMET has not been studied. The systemic clearance and Cmax of sumatriptan were similar in black (n = 34) and Caucasian (n = 38) healthy male subjects.

Drug Interactions

No formal drug interaction studies have been conducted with TREXIMET.

Monoamine Oxidase Inhibitors: TREXIMET is contraindicated in patients taking MAO-A inhibitors (see CONTRAINDICATIONS and PRECAUTIONS: Drug Interactions). Treatment with MAO-A inhibitors generally leads to an increase of sumatriptan plasma levels. This interaction has not been seen with an MAO-B inhibitor.

Alcohol: The effect of alcohol consumption on the pharmacokinetics of TREXIMET has not been studied. Alcohol consumed 30 minutes prior to sumatriptan ingestion had no effect on the pharmacokinetics of sumatriptan.

CLINICAL TRIALS

The efficacy of TREXIMET in providing relief from migraine was demonstrated in 2 randomized, double-blind, multicenter, parallel-group trials utilizing placebo and each individual active component of TREXIMET (sumatriptan and naproxen sodium) as comparison treatments. Patients enrolled in these 2 trials were predominately female (87%) and Caucasian (88%), with a mean age of 40 years (range 18 to 65 years). Patients were instructed to treat a migraine of moderate to severe pain with 1 tablet. No rescue medication was allowed within 2 hours postdose. Patients evaluated their headache pain 2 hours after taking 1 dose of study medication; headache relief was defined as a reduction in headache severity from moderate or severe pain to mild or no pain. Associated symptoms of nausea, photophobia, and phonophobia were also evaluated. Sustained pain free was defined as a reduction in headache severity from moderate or severe pain to no pain at 2 hours postdose without a return of mild, moderate, or severe pain and no use of rescue medication for 24 hours postdose. The results from the 2 controlled clinical trials are summarized in Table 1. In both trials, the percentage of patients achieving headache pain relief 2 hours after treatment was significantly greater among patients receiving TREXIMET (65% and 57%) compared with those who received placebo (28% and 29%).

Further, the percentage of patients who remained pain free without use of other medications through 24 hours postdose was significantly greater among patients receiving a single dose of TREXIMET (25% and 23%) compared with those who received placebo (8% and 7%) or either sumatriptan (16% and 14%) or naproxen sodium (10%) alone.

Table 1. Percentage of Patients With 2-Hour Pain Relief and Sustained Pain Free Following Treatmenta
 | TREXIMET | Sumatriptan; 85 mg | Naproxen Sodium; 500 mg | Placebo
2-Hour Pain Relief
Study 1 (all patients) | 65%b; n = 364 | 55%; n = 361 | 44%; n = 356 | 28%; n = 360
Study 2 (all patients) | 57%b; n = 362 | 50%; n = 362 | 43%; n = 364 | 29%; n = 382
Sustained Pain Free (2-24 Hours)
Study 1 | 25%c; n = 364 | 16%; n = 361 | 10%; n = 356 | 8%; n = 360
Study 2 | 23%c; n = 362 | 14%; n = 362 | 10%; n = 364 | 7%; n = 382
ap values provided only for prespecified comparisons.
bp<0.05 versus placebo and sumatriptan.
cp<0.01 versus placebo, sumatriptan, and naproxen sodium.

Note that comparisons of the performance of different drugs based upon results obtained in different clinical trials are never reliable. Because studies are generally conducted at different times, with different samples of patients, by different investigators, employing different criteria and/or different interpretations of the same criteria, under different conditions (dose, dosing regimen, etc.), quantitative estimates of treatment response and the timing of response may be expected to vary considerably from study to study.

The percentage of patients achieving initial headache pain relief within 2 hours following treatment with TREXIMET is shown in Figure 1.

Figure 1. Percentage of Patients With Initial Headache Pain Relief Within 2 Hours

Compared with placebo, there was a decreased incidence of photophobia, phonophobia, and nausea 2 hours after the administration of TREXIMET. The estimated probability of taking a rescue medication over the first 24 hours is shown in Figure 2.

Figure 2. Cumulative Percentage of Subjects Taking a Rescue Medication Over the 24 Hours Following the First Dosea

aPlot also includes patients who had no response to the initial dose.

TREXIMET was more effective than placebo regardless of the presence of aura; duration of headache prior to treatment; gender, age, or weight of the patient; or concomitant use of oral contraceptives or common migraine prophylactic drugs (e.g., beta-blockers, anti-epileptic drugs, tricyclic antidepressants).

INDICATIONS AND USAGE

TREXIMET is indicated for the acute treatment of migraine attacks with or without aura in adults. Carefully consider the potential benefits and risks of TREXIMET and other treatment options when deciding to use TREXIMET.

TREXIMET is not intended for the prophylactic therapy of migraine or for use in the management of hemiplegic or basilar migraine (see CONTRAINDICATIONS). Safety and effectiveness of TREXIMET have not been established for cluster headache.

CONTRAINDICATIONS

Cardiac, Cerebrovascular, or Peripheral Vascular Disease

TREXIMET should not be given to patients with history, symptoms, or signs of ischemic cardiac, cerebrovascular, or peripheral vascular syndromes. In addition, patients with other significant underlying cardiovascular diseases should not receive TREXIMET, nor should patients who have had coronary artery bypass graft (CABG) surgery. Ischemic cardiac syndromes include, but are not limited to, angina pectoris of any type (e.g., stable angina of effort and vasospastic forms of angina, such as the Prinzmetal variant), all forms of myocardial infarction, and silent myocardial ischemia. Cerebrovascular syndromes include, but are not limited to, strokes of any type as well as transient ischemic attacks. Peripheral vascular disease includes, but is not limited to, ischemic bowel disease (see WARNINGS: Cardiovascular Effects).

Uncontrolled Hypertension

TREXIMET should not be given to patients with uncontrolled hypertension because the components have been shown to increase blood pressure.

Monoamine Oxidase-A Inhibitors

Concurrent administration of MAO-A inhibitors or use of TREXIMET within 2 weeks of discontinuation of MAO-A inhibitor therapy is contraindicated (see CLINICAL PHARMACOLOGY: Drug Interactions and PRECAUTIONS: Drug Interactions).

Ergotamine-Containing or Ergot-Type Medications

TREXIMET and any ergotamine-containing or ergot-type medication (like dihydroergotamine or methysergide) should not be used within 24 hours of each other (see PRECAUTIONS: Drug Interactions).

Other 5-HT 1 Agonists

Since TREXIMET contains sumatriptan, it should not be administered within 24 hours of another 5-HT1 agonist.

Hemiplegic or Basilar Migraine

TREXIMET should not be administered to patients with hemiplegic or basilar migraine.

Hepatic Impairment

TREXIMET is contraindicated in patients with hepatic impairment (see CLINICAL PHARMACOLOGY: Special Populations, PRECAUTIONS: Hepatic Effects, and PRECAUTIONS: Geriatric Use).

Allergy to Naproxen/Asthma, Nasal Polyps, Urticaria, and Hypotension Associated With Nonsteroidal Anti-inflammatory Drugs

TREXIMET is contraindicated in patients who have had allergic reactions to prescription as well as to over-the-counter products containing naproxen. It is also contraindicated in patients in whom aspirin or other nonsteroidal anti-inflammatory/analgesic drugs induce the syndrome of asthma, rhinitis, and nasal polyps. Anaphylactic/anaphylactoid reactions to naproxen, whether of the true allergic type or the pharmacologic idiosyncratic type (e.g., aspirin hypersensitivity syndrome), usually but not always occur in patients with a known history of such reactions. Both types of reactions have the potential of being fatal. Therefore, careful questioning of patients for medical conditions such as asthma, nasal polyps, urticaria, and hypotension associated with NSAIDs before starting therapy is important. In addition, if such symptoms occur during therapy, treatment should be discontinued (see WARNINGS: Anaphylactic/Anaphylactoid Reactions and PRECAUTIONS: Preexisting Asthma).

Hypersensitivity to Sumatriptan or Naproxen

TREXIMET is contraindicated in patients with hypersensitivity to sumatriptan, naproxen, or any other component of the product.

WARNINGS

TREXIMET should only be used where a clear diagnosis of migraine headache has been established.

Cardiovascular Effects

Risk of Myocardial Ischemia and/or Infarction and Other Adverse Cardiac Events: TREXIMET should not be given to patients with documented ischemic or vasospastic coronary artery disease (CAD) or to patients with a history of CABG surgery (see CONTRAINDICATIONS). It is strongly recommended that sumatriptan-containing products not be given to patients in whom unrecognized CAD is predicted by the presence of risk factors (e.g., hypertension, hypercholesterolemia, smoker, obesity, diabetes, strong family history of CAD, female with surgical or physiological menopause, male over 40 years of age) unless a cardiovascular evaluation provides satisfactory clinical evidence that the patient is reasonably free of CAD and ischemic myocardial disease or other significant underlying cardiovascular disease. The sensitivity of cardiac diagnostic procedures to detect cardiovascular disease or predisposition to coronary artery vasospasm is modest, at best. If, during the cardiovascular evaluation, the patient’s medical history or electrocardiographic investigations reveal findings indicative of, or consistent with, coronary artery vasospasm or myocardial ischemia, TREXIMET should not be administered (see CONTRAINDICATIONS).

For patients with risk factors predictive of CAD who are determined to have a satisfactory cardiovascular evaluation, it is strongly recommended that administration of the first dose of TREXIMET take place in the setting of a physician’s office or similar medically staffed and equipped facility unless the patient has previously received sumatriptan. Because cardiac ischemia can occur in the absence of clinical symptoms, consideration should be given to obtaining an electrocardiogram (ECG) immediately following first-time use of TREXIMET in patients with risk factors.

It is recommended that patients who are intermittent long-term users of TREXIMET and who have or acquire risk factors predictive of CAD as described above undergo periodic cardiovascular evaluation as they continue to use TREXIMET.

The systematic approach described above is intended to reduce the likelihood that patients with unrecognized cardiovascular disease will be inadvertently exposed to sumatriptan-containing products.

Cardiac Events and Fatalities Associated With 5-HT1 Agonists: Serious adverse cardiac events, including acute myocardial infarction, life-threatening disturbances of cardiac rhythm, and death have been reported within a few hours following the administration of sumatriptan. Considering the extent of use of 5-HT1 agonists in patients with migraine, the incidence of these events is extremely low.

The fact that sumatriptan can cause coronary vasospasm, that some of these events have occurred in patients with no prior cardiac disease history and with documented absence of CAD, and the close proximity of the events to sumatriptan use support the conclusion that some of these cases were caused by the drug. In cases, however, where there has been known underlying coronary artery disease, the relationship is uncertain.

Cardiovascular Thrombotic Events and Fatalities Associated With Nonsteroidal Anti-inflammatory Drugs: Clinical trials of several COX-2 selective and nonselective NSAIDs of up to 3 years' duration have shown an increased risk of serious cardiovascular thrombotic events, myocardial infarction, and stroke, which can be fatal. All NSAIDs, both COX-2 selective and nonselective, may have a similar risk. Patients with known cardiovascular disease or risk factors for cardiovascular disease may be at greater risk. To minimize the potential risk for an adverse cardiovascular event in patients treated with an NSAID, the lowest effective dose should be used for the shortest duration possible. Physicians and patients should remain alert for the development of such events, even in the absence of previous cardiovascular symptoms. Patients should be informed about the signs and/or symptoms of serious cardiovascular events and the steps to take if they occur.

There is no consistent evidence that concurrent use of aspirin mitigates the increased risk of serious cardiovascular thrombotic events associated with NSAID use. The concurrent use of aspirin and an NSAID does increase the risk of serious gastrointestinal events (see WARNINGS: Risk of Gastrointestinal Ulceration, Bleeding, and Perforation With Nonsteroidal Anti-inflammatory Drug Therapy).

Premarketing Experience With TREXIMET: Among 3,302 patients with migraine who received TREXIMET in premarketing controlled and uncontrolled clinical trials, a 47-year-old female with cardiac risk factors in an open-label 12-month safety study experienced signs and symptoms of acute coronary syndrome approximately 2 hours after receiving TREXIMET.

Drug-Associated Cerebrovascular Events and Fatalities: Cerebral hemorrhage, subarachnoid hemorrhage, stroke, and other cerebrovascular events have been reported in patients treated with oral or subcutaneous sumatriptan, and some have resulted in fatalities. The relationship of sumatriptan to these events is uncertain. In a number of cases, it appears possible that the cerebrovascular events were primary, sumatriptan having been administered in the incorrect belief that the symptoms experienced were a consequence of migraine when they were not. As with other acute migraine therapies, before treating headaches in patients not previously diagnosed as migraineurs, and in migraineurs who present with atypical symptoms, care should be taken to exclude other potentially serious neurological conditions. It should also be noted that patients with migraine may be at increased risk of certain cerebrovascular events (e.g., cerebrovascular accident, transient ischemic attack).

Other Vasospasm-Related Events: Sumatriptan may cause vasospastic reactions other than coronary artery vasospasm. Both peripheral vascular ischemia and colonic ischemia with abdominal pain and bloody diarrhea have been reported. Transient and permanent blindness and significant partial vision loss have been reported with the use of sumatriptan. Visual disorders may also be part of a migraine attack.

Increase in Blood Pressure: TREXIMET is contraindicated in patients with uncontrolled hypertension (see CONTRAINDICATIONS). TREXIMET should be used with caution in patients with controlled hypertension.

Significant elevation in blood pressure, including hypertensive crisis, has been reported in patients with and without a history of hypertension receiving sumatriptan. Sumatriptan-containing products should be administered with caution to patients with controlled hypertension as transient increases in blood pressure and peripheral vascular resistance have been observed.

NSAID-containing products can lead to onset of new hypertension or worsening of preexisting hypertension, either of which may contribute to the increased incidence of cardiovascular events. Patients taking thiazides or loop diuretics may have impaired response to these therapies when taking NSAIDs. The potential effect on blood pressure associated with long-term use of TREXIMET has not been studied. Blood pressure should be monitored closely during the initiation of NSAID treatment and throughout the course of therapy.

Congestive Heart Failure and Edema: TREXIMET should be used with caution in patients with fluid retention or heart failure. Fluid retention and edema have been observed in some patients taking NSAIDs. Since each TREXIMET tablet contains 61.2 mg of sodium (about 2.7 mEq/500 mg of naproxen sodium), this should be considered in patients whose overall intake of sodium must be severely restricted.

Serotonin Syndrome

The development of a potentially life-threatening serotonin syndrome may occur with triptans, including treatment with TREXIMET, particularly during combined use with selective serotonin reuptake inhibitors (SSRIs) or serotonin norepinephrine reuptake inhibitors (SNRIs). If concomitant treatment with TREXIMET and an SSRI (e.g., fluoxetine, paroxetine, sertraline, fluvoxamine, citalopram, escitalopram) or SNRI (e.g., venlafaxine, duloxetine) is clinically warranted, careful observation of the patient is advised, particularly during treatment initiation and dose increases. Serotonin syndrome symptoms may include mental status changes (e.g., agitation, hallucinations, coma), autonomic instability (e.g., tachycardia, labile blood pressure, hyperthermia), neuromuscular aberrations (e.g., hyperreflexia, incoordination), and/or gastrointestinal symptoms (e.g., nausea, vomiting, diarrhea) (see PRECAUTIONS: Drug Interactions).

Risk of Gastrointestinal Ulceration, Bleeding, and Perforation With Nonsteroidal Anti-inflammatory Drug Therapy

TREXIMET contains an NSAID. NSAID-containing products can cause serious gastrointestinal adverse events including inflammation, bleeding, ulceration, and perforation of the stomach, small intestine, or large intestine, which can be fatal.

These serious adverse events can occur at any time, with or without warning symptoms, in patients treated with NSAIDs. Only 1 in 5 patients who develop a serious upper gastrointestinal adverse event on NSAID therapy is symptomatic. Upper gastrointestinal ulcers, gross bleeding, or perforation caused by NSAIDs appear to occur in approximately 1% of patients treated daily for 3 to 6 months and in about 2% to 4% of patients treated for 1 year. These trends continue with longer duration of use, increasing the likelihood of developing a serious gastrointestinal event at some time during the course of therapy. However, even short-term therapy is not without risk. Among 3,302 patients with migraine who received TREXIMET in premarketing controlled and uncontrolled clinical trials, 1 patient experienced a recurrence of gastric ulcer after taking 8 doses over 3 weeks, and 1 patient developed a gastric ulcer after treating an average of 8 attacks per month over 7 months.

NSAID-containing products, including TREXIMET, should be prescribed with extreme caution in those with a prior history of ulcer disease or gastrointestinal bleeding. Patients with a prior history of peptic ulcer disease and/or gastrointestinal bleeding who use NSAIDs have a greater than 10-fold increased risk for developing gastrointestinal bleeding compared to patients with neither of these risk factors. Other factors that increase the risk for gastrointestinal bleeding in patients treated with NSAIDs include concomitant use of oral corticosteroids or anticoagulants, longer duration of NSAID therapy, smoking, use of alcohol, older age, and poor general health status. Most spontaneous reports of fatal gastrointestinal events are in elderly or debilitated patients, and therefore special care should be taken in treating this population.

To minimize the potential risk for an adverse gastrointestinal event in patients treated with an NSAID-containing product, the lowest effective dose should be used for the shortest possible duration. Patients and physicians should remain alert for signs and symptoms of gastrointestinal ulceration and bleeding during NSAID therapy and promptly initiate additional evaluation and treatment if a serious gastrointestinal adverse event is suspected. This should include discontinuation of the NSAID until a serious gastrointestinal adverse event is ruled out. For high-risk patients, alternate therapies that do not involve NSAIDs should be considered.

NSAIDs should be given with care to patients with a history of inflammatory bowel disease (ulcerative colitis, Crohn's disease) as their condition may be exacerbated.

Renal Effects

Long-term administration of NSAIDs has resulted in renal papillary necrosis and other renal injury. Renal toxicity has also been seen in patients in whom renal prostaglandins have a compensatory role in the maintenance of renal perfusion. In these patients administration of an NSAID may cause a dose-dependent reduction in prostaglandin formation and, secondarily, in renal blood flow, which may precipitate overt renal decompensation. Patients at greatest risk of this reaction are those with impaired renal function, heart failure, liver dysfunction, those taking diuretics and angiotensin-converting enzyme (ACE) inhibitors, and the elderly. Discontinuation of NSAID therapy is usually followed by recovery to the pretreatment state.

Advanced Renal Disease: Treatment with TREXIMET is not recommended in patients with advanced renal disease. If therapy with TREXIMET must be initiated, close monitoring of the patient’s renal function is advisable (see CLINICAL PHARMACOLOGY: Pharmacokinetics and PRECAUTIONS: Renal Effects). No information is available from controlled clinical studies regarding the use of TREXIMET in patients with advanced renal disease.

Anaphylactic/Anaphylactoid Reactions

As with other NSAID-containing products, anaphylactic/anaphylactoid reactions may occur in patients without known prior exposure to naproxen. TREXIMET should not be given to patients with the aspirin triad. This symptom complex typically occurs in patients with asthma who experience rhinitis with or without nasal polyps, or who exhibit severe, potentially fatal bronchospasm after taking aspirin or other NSAIDs (see CONTRAINDICATIONS, PRECAUTIONS: Preexisting Asthma, and PRECAUTIONS: Drug Interactions).

Anaphylactic/anaphylactoid reactions have occurred in patients receiving sumatriptan. Such reactions can be life-threatening or fatal. In general, anaphylactic reactions to drugs are more likely to occur in individuals with a history of sensitivity to multiple allergens (see CONTRAINDICATIONS). Emergency help should be sought in cases where an anaphylactoid reaction occurs. Anaphylactoid reactions, like anaphylaxis, may have a fatal outcome.

Skin Reactions

NSAID-containing products, including TREXIMET, can cause serious adverse events such as exfoliative dermatitis, Stevens-Johnson syndrome, and toxic epidermal necrolysis, which can be fatal. These serious events may occur without warning. Patients should be informed about the signs and symptoms of serious skin manifestations and use of the drug should be discontinued at the first appearance of skin rash or any other sign of hypersensitivity.

Pregnancy

TREXIMET should not be used in late pregnancy because NSAID-containing products have been shown to cause premature closure of the ductus arteriosus. TREXIMET should not be used during early pregnancy unless the potential benefit justifies the potential risk to the fetus (see PRECAUTIONS: Pregnancy).

PRECAUTIONS

Naproxen-Containing Products

TREXIMET and other naproxen-containing products should not be used concomitantly since they all circulate in the plasma as the naproxen anion.

Chest, Jaw, or Neck Pain/Discomfort

Chest discomfort and jaw or neck tightness have been reported following use of sumatriptan. Only rarely have these symptoms been associated with ischemic ECG changes. However, because sumatriptan may cause coronary artery vasospasm, patients who experience signs or symptoms suggestive of angina following TREXIMET should be evaluated for the presence of CAD or a predisposition to Prinzmetal variant angina before receiving additional doses of TREXIMET and should be monitored electrocardiographically if dosing is resumed and similar symptoms recur. Similarly, patients who experience other symptoms or signs suggestive of decreased arterial flow, such as ischemic bowel syndrome or Raynaud syndrome, following TREXIMET should be evaluated for atherosclerosis or predisposition to vasospasm (see WARNINGS: Cardiovascular Effects).

Diseases That May Alter the Absorption, Metabolism, or Excretion of Drugs

TREXIMET should also be administered with caution to patients with diseases that may alter the absorption, metabolism, or excretion of drugs, such as impaired renal function.

Seizures

TREXIMET should be used with caution in patients with a history of epilepsy or conditions associated with a lowered seizure threshold. There have been reports of seizure following administration of sumatriptan.

Other Potentially Serious Neurologic Conditions

Care should be taken to exclude other potentially serious neurologic conditions before treating headache in patients not previously diagnosed with migraine headache or who experience a headache that is atypical for them. There have been reports where patients received sumatriptan for severe headaches that were subsequently shown to have been secondary to an evolving neurologic lesion (see WARNINGS: Drug-Associated Cerebrovascular Events and Fatalities). For a given attack, if a patient does not respond to the first dose of TREXIMET, the diagnosis of migraine should be reconsidered before administration of a second dose.

Hepatic Effects

TREXIMET is contraindicated in patients with hepatic impairment (see CONTRAINDICATIONS and CLINICAL PHARMACOLOGY).A patient with symptoms and/or signs suggesting liver dysfunction or in whom an abnormal liver test has occurred should be evaluated for evidence of the development of a more severe hepatic reaction while on therapy with TREXIMET. Borderline elevations of 1 or more liver tests may occur in up to 15% of patients who take NSAID-containing products. These abnormalities may progress, may remain essentially unchanged, or may be transient with continued therapy. Notable (3 times the upper limit of normal) elevations of SGPT (ALT) or SGOT (AST) have been reported in approximately 1% of patients in clinical trials with NSAIDs. In addition, cases of severe hepatic reactions, including jaundice and fatal fulminant hepatitis, liver necrosis, and hepatic failure, some of them with fatal outcomes, have been reported with NSAIDs. A patient with symptoms and/or signs suggesting liver dysfunction, or in whom an abnormal liver test has occurred, should be evaluated for evidence of the development of a more severe hepatic reaction while on therapy with TREXIMET. If clinical signs and symptoms consistent with liver disease develop, or if systemic manifestations occur (e.g., eosinophilia, rash), TREXIMET should be discontinued.

Overuse

Overuse of acute migraine treatments has been associated with the exacerbation of headache (medication overuse headache) in susceptible patients. Withdrawal of the treatment may be necessary.

Binding to Melanin-Containing Tissues

In rats treated with a single subcutaneous dose (0.5 mg/kg) or oral dose (2 mg/kg) of radiolabeled sumatriptan, the elimination half-life of radioactivity from the eye was 15 and 23 days, respectively, suggesting that sumatriptan and/or its metabolites bind to the melanin of the eye. Because there could be an accumulation in melanin-rich tissues over time, sumatriptan could possibly cause toxicity in these tissues after extended use. However, no effects on the retina related to treatment with sumatriptan were noted in any of the oral or subcutaneous toxicity studies. Although no systematic monitoring of ophthalmologic function was undertaken in clinical trials and no specific recommendations for ophthalmologic monitoring are offered, prescribers should be aware of the possibility of long-term ophthalmologic effects.

Corneal Opacities

Sumatriptan causes corneal opacities and defects in the corneal epithelium in dogs (see ANIMAL TOXICOLOGY). Adverse eye findings have also been observed in animal studies with some NSAIDs. Patients were not systematically evaluated for these changes in clinical trials. However, since the animal findings raise the possibility that adverse effects on the eye may occur in humans, it is recommended that ophthalmic studies be carried out if any change or disturbance in vision occurs.

Renal Effects

Caution is recommended in patients with preexisting kidney disease or dehydration (see WARNINGS: Renal Effects). Naproxen and its metabolites are eliminated primarily by the kidneys; therefore, TREXIMET should be used with caution in patients with significantly impaired renal function, and monitoring of serum creatinine and/or creatinine clearance is advised in these patients. TREXIMET is not recommended for use in patients with creatinine clearance less than 30 mL/min (see CLINICAL PHARMACOLOGY: Special Populations).

Hematological Effects

Patients on long-term treatment with NSAIDs, including TREXIMET, should have their hemoglobin or hematocrit checked if they exhibit any signs or symptoms of anemia. Anemia is sometimes seen in patients receiving NSAIDs. This may be due to fluid retention, occult or gross gastrointestinal blood loss, or an incompletely described effect upon erythropoiesis. Patients receiving TREXIMET who may be adversely affected by alterations in platelet function, such as those with coagulation disorders or patients receiving anticoagulants, should be carefully monitored. NSAID-containing products inhibit platelet aggregation and have been shown to prolong bleeding time in some patients. Unlike aspirin, their effect on platelet function is quantitatively less, of shorter duration, and reversible.

Preexisting Asthma

Patients with asthma may have aspirin-sensitive asthma. The use of aspirin in patients with aspirin-sensitive asthma has been associated with severe bronchospasm that can be fatal. Since cross reactivity, including bronchospasm, between aspirin and other NSAIDs has been reported in such aspirin-sensitive patients, TREXIMET should not be administered to patients with this form of aspirin sensitivity and should be used with caution in patients with preexisting asthma.

Information for Patients

Patients should be informed of the following information before initiating therapy with TREXIMET and periodically during the course of ongoing therapy. Patients should also be encouraged to read the Medication Guide that accompanies each prescription dispensed.

1. TREXIMET may cause serious cardiovascular side effects such as myocardial infarction or stroke, which may result in hospitalization and even death. Although serious cardiovascular events can occur without warning symptoms, patients should be alert for the signs and symptoms of chest pain, shortness of breath, weakness, slurring of speech, and should ask for medical advice when observing any indicative sign or symptoms. Patients should be apprised of the importance of this follow-up (see WARNINGS: Cardiovascular Effects).
2. TREXIMET, like other NSAID-containing products, may cause gastrointestinal discomfort and, rarely, serious gastrointestinal side effects such as ulcers and bleeding, which may result in hospitalization and even death. Although serious gastrointestinal tract ulcerations and bleeding can occur without warning symptoms, patients should be alert for the signs and symptoms of ulcerations and bleeding and should ask for medical advice when observing any indicative sign or symptoms, including epigastric pain, dyspepsia, melena, and hematemesis. Patients should be apprised of the importance of this follow-up (see WARNINGS: Risk of Gastrointestinal Ulceration, Bleeding, and Perforation With Nonsteroidal Anti-inflammatory Drug Therapy).
3. TREXIMET, like other NSAID-containing products, may increase the risk of serious skin side effects such as exfoliative dermatitis, Stevens-Johnson syndrome, and toxic epidermal necrolysis, which may result in hospitalizations and even death. Although serious skin reactions may occur without warning, patients should be alert for the signs and symptoms of skin rash and blisters, fever, or other signs of hypersensitivity such as itching and should ask for medical advice when observing any indicative signs or symptoms. Patients should be advised to stop the drug immediately if they develop any type of rash and contact their physicians as soon as possible.
4. Patients should promptly report signs or symptoms of unexplained weight gain or edema to their physicians.
5. Patients should be informed of the warning signs and symptoms of hepatotoxicity (e.g., nausea, fatigue, lethargy, pruritus, jaundice, right upper quadrant tenderness, flu-like symptoms). If these occur, patients should be instructed to stop therapy and seek immediate medical therapy.
6. Patients should be informed of the signs of an anaphylactic/anaphylactoid reaction (e.g., difficulty breathing, swelling of the face or throat). If these occur, patients should be instructed to seek immediate emergency help (see WARNINGS: Anaphylactic/Anaphylactoid Reactions).
7. TREXIMET should not be used in late pregnancy because NSAID-containing products have been shown to cause premature closure of the ductus arteriosus. TREXIMET should not be used during early pregnancy unless the potential benefit justifies the potential risk to the fetus.
8. Patients should be cautioned about the risk of serotonin syndrome, particularly during concomitant use with SSRIs or SNRIs.
9. Caution should be exercised by patients whose activities require alertness if they experience drowsiness, dizziness, vertigo, or depression during therapy with TREXIMET.

Laboratory Tests

Because serious gastrointestinal tract ulcerations and bleeding can occur without warning symptoms, physicians should monitor for signs or symptoms of gastrointestinal bleeding. If clinical signs and symptoms consistent with liver or renal disease develop, systemic manifestations occur (e.g., eosinophilia, rash), or abnormal liver tests persist or worsen, TREXIMET should be discontinued.

Drug Interactions

Monoamine Oxidase-A Inhibitors: The use of TREXIMET in patients receiving MAO-A inhibitors is contraindicated (see CLINICAL PHARMACOLOGY: Drug Interactions and CONTRAINDICATIONS). MAO-A inhibitors reduce sumatriptan clearance, significantly increasing systemic exposure. In patients taking MAO-A inhibitors, sumatriptan plasma levels attained after treatment with recommended doses are 7-fold higher following oral administration than those obtained under other conditions.

Ergot-Containing Drugs: Ergot-containing drugs have been reported to cause prolonged vasospastic reactions. Because there is a theoretical basis that these effects may be additive, use of ergotamine-containing or ergot-type medications (e.g., dihydroergotamine, methysergide) and TREXIMET within 24 hours of each other should be avoided (see CONTRAINDICATIONS).

Methotrexate: Caution should be used if TREXIMET is administered concomitantly with methotrexate. Naproxen sodium and other NSAIDs have been reported to reduce the tubular secretion of methotrexate in an animal model, possibly increasing the toxicity of methotrexate. Concomitant administration of some NSAIDs with high-dose methotrexate therapy has been reported to elevate and prolong serum methotrexate levels, resulting in deaths from severe hematologic and gastrointestinal toxicity.

Aspirin: When naproxen is administered with aspirin, its protein binding is reduced, although the clearance of free naproxen is not altered. The clinical significance of this interaction is not known; however, as with other NSAID-containing products, concomitant administration of TREXIMET and aspirin is not generally recommended because of the potential of increased adverse effects.

Selective Serotonin Reuptake Inhibitors/Serotonin Norepinephrine Reuptake Inhibitors and Serotonin Syndrome: Cases of life-threatening serotonin syndrome have been reported during combined use of SSRIs or SNRIs and triptans (see WARNINGS: Serotonin Syndrome).

Angiotensin-Converting Enzyme Inhibitors: Reports suggest that NSAIDs may diminish the antihypertensive effect of ACE inhibitors. The use of TREXIMET in patients who are receiving ACE inhibitors may potentiate renal disease states (see WARNINGS: Renal Effects).

Furosemide: Clinical studies, as well as postmarketing observations, have shown that NSAIDs can reduce the natriuretic effect of furosemide and thiazides in some patients. This response has been attributed to inhibition of renal prostaglandin synthesis. During concomitant therapy with NSAIDs, the patient should be observed closely for signs of renal failure (see WARNINGS: Renal Effects), as well as to assure diuretic efficacy.

Lithium: NSAIDs have produced an elevation of plasma lithium levels and a reduction in renal lithium clearance. The mean minimum lithium concentration increased 15%, and the renal clearance was decreased by approximately 20%. These effects have been attributed to inhibition of renal prostaglandin synthesis by the NSAID. Thus, when TREXIMET and lithium are administered concurrently, patients should be observed carefully for signs of lithium toxicity.

Probenecid: Probenecid given concurrently increases naproxen anion plasma levels and extends its plasma half-life significantly.

Propranolol and Other Beta-Blockers: Propranolol 80 mg given twice daily had no significant effect on sumatriptan pharmacokinetics. Naproxen and other NSAIDs can reduce the antihypertensive effect of propranolol and other beta-blockers.

Warfarin: The effects of warfarin and NSAIDs on gastrointestinal bleeding are synergistic, such that patients taking both drugs have a higher risk of serious gastrointestinal bleeding than patients taking either drug alone.

Drug/Laboratory Test Interactions

The ability of TREXIMET to interfere with commonly employed clinical laboratory tests has not been investigated.

Sumatriptan is not known to interfere with commonly employed clinical laboratory tests. Naproxen may decrease platelet aggregation and prolong bleeding time. This effect should be kept in mind when bleeding times are determined.

The administration of naproxen sodium may result in increased urinary values for 17-ketogenic steroids because of an interaction between the drug and/or its metabolites with m-di-nitrobenzene used in this assay. Although 17-hydroxy-corticosteroid measurements (Porter-Silber test) do not appear to be artifactually altered, it is suggested that therapy with naproxen be temporarily discontinued 72 hours before adrenal function tests are performed if the Porter-Silber test is to be used.

Naproxen may interfere with some urinary assays of 5-hydroxy indoleacetic acid (5HIAA).

Carcinogenesis, Mutagenesis, Impairment of Fertility

Carcinogenesis: The carcinogenic potential of TREXIMET has not been studied.

The carcinogenic potential of sumatriptan was evaluated in oral carcinogenicity studies in mice (78 weeks) and rats (104 weeks). The highest dose administered to mice and rats (160 mg/kg/day) is approximately 9 and 18 times, respectively, the recommended human oral daily dose of 85 mg sumatriptan on a mg/m^2 basis. There was no evidence of an increase in tumors in either species related to sumatriptan administration.

The carcinogenic potential of naproxen sodium was evaluated in a 2-year oral carcinogenicity study in rats at doses of 8, 16, and 24 mg/kg/day and in another 2-year oral carcinogenicity study in rats at a dose of 8 mg/kg/day. No evidence of tumorigenicity was found in either study, at doses up to approximately 0.5 times the recommended human oral daily dose of 500 mg/day naproxen sodium on a mg/m^2 basis.

Mutagenesis: Sumatriptan and naproxen sodium tested alone and in combination were negative in an in vitro bacterial reverse mutation assay, and in an in vivo micronucleus assay in mice.

The combination of sumatriptan and naproxen sodium was negative in an in vitro mouse lymphoma tk assay in the presence and absence of metabolic activation. However, in separate in vitro mouse lymphoma tk assays, naproxen sodium alone was reproducibly positive in the presence of metabolic activation.

Naproxen sodium alone and in combination with sumatriptan was positive in an in vitro clastogenicity assay in mammalian cells in the presence and absence of metabolic activation. The clastogenic effect for the combination was reproducible within this assay and was greater than observed with naproxen sodium alone. Sumatriptan alone was negative in these assays.

Chromosomal aberrations were not induced in peripheral blood lymphocytes following 7 days of twice-daily dosing with TREXIMET in human volunteers.

In previous studies, sumatriptan alone was not mutagenic in 2 gene mutation assays (the Ames test and the in vitro Chinese Hamster V79/HGPRT assay) and was not clastogenic in 2 cytogenetics assays (the in vitro human lymphocyte assay and the in vivo rat micronucleus assay).

Impairment of Fertility: The effect of TREXIMET on fertility in animals has not been studied.

In a study in which male and female rats were dosed daily with oral sumatriptan prior to and throughout the mating period, there was a treatment-related decrease in fertility secondary to a decrease in mating in animals treated with 50 and 500 mg/kg/day. The highest no-effect dose for this finding was 5 mg/kg/day, or approximately 0.5 times the recommended human oral daily dose of 85 mg sumatriptan on a mg/m^2 basis. It is not clear whether the problem is associated with treatment of the males or females or both combined. In a similar study of sumatriptan by the subcutaneous route there was no evidence of impaired fertility at doses up to 60 mg/kg/day.

Pregnancy

Pregnancy Category C. In developmental toxicity studies in rabbits, oral treatment with sumatriptan combined with naproxen sodium (5/9, 25/45, or 50/90 mg/kg/day sumatriptan/naproxen sodium) or each drug alone (50/0 or 0/90 mg/kg/day sumatriptan/naproxen sodium) resulted in decreased fetal body weight in all treated groups and in increased embryofetal death at the highest dose of naproxen, alone and in combination with sumatriptan. Naproxen sodium, alone and in combination with sumatriptan, increased the total incidences of fetal abnormalities at all doses and increased the incidences of specific malformations (cardiac interventricular septal defect in the 50/90-mg/kg/day group, fused caudal vertebrae in the 50/0- and 0/90-mg/kg/day groups) and variations (absent intermediate lobe of the lung, irregular ossification of the skull, incompletely ossified sternal centra) in the 50/0- and 0/90-mg/kg/day groups. A no-effect dose for development toxicity in rabbits was not established. The lowest effect dose was 5/9 mg/kg/day sumatriptan/naproxen sodium, which was associated with plasma exposures (AUC) to sumatriptan and naproxen that were 1.4 and 0.14 times, respectively, those attained at the maximum recommended human oral daily dose of 85 mg sumatriptan and 500 mg naproxen sodium.

In previous developmental toxicity studies in rats and rabbits, oral treatment with sumatriptan was associated with embryolethality, fetal abnormalities, and pup mortality. Oral treatment of pregnant rats with sumatriptan during the period of organogenesis resulted in an increased incidence of fetal blood vessel (cervicothoracic and umbilical) abnormalities and decreased pup survival at doses of 250 mg/kg/day or higher. The highest no-effect dose was approximately 60 mg/kg/day, which is approximately 7 times the recommended human oral daily dose of 85 mg sumatriptan on a mg/m^2 basis. Oral treatment of pregnant rabbits with sumatriptan during the period of organogenesis resulted in an increased incidence of cervicothoracic vascular and skeletal abnormalities at a dose of 50 mg/kg/day and embryolethality at 100 mg/kg/day. The highest no-effect dose for embryotoxicity in rabbits was 15 mg/kg/day, or approximately 3 times the recommended human oral daily dose of 85 mg sumatriptan on a mg/m^2 basis.

Inhibitors of prostaglandin synthesis (including naproxen) are known to delay parturition. Because of this and the known effects of drugs of this class on the human fetal cardiovascular system (closure of the ductus arteriosus), use during third trimester should be avoided.

There are no adequate and well-controlled studies in pregnant women.

TREXIMET should not be used during pregnancy unless the potential benefit justifies the potential risk to the fetus.

Pregnancy Registry: To monitor fetal outcomes of pregnant women exposed to TREXIMET, GlaxoSmithKline maintains a TREXIMET Pregnancy Registry. Physicians are encouraged to register patients as soon as possible after they become pregnant and (if possible) before the outcome of the pregnancy is known by calling (800) 336-2176.

Labor and Delivery

In rat studies with NSAIDs, as with other drugs known to inhibit prostaglandin synthesis, an increased incidence of dystocia, delayed parturition, and decreased pup survival occurred. Naproxen-containing products are not recommended in labor and delivery because, through its prostaglandin synthesis inhibitory effect, naproxen may adversely affect fetal circulation and inhibit uterine contractions, thus increasing the risk of uterine hemorrhage.

Nursing Mothers

Both active components of TREXIMET, sumatriptan and naproxen sodium, have been reported to be excreted in human breast milk. Because of the possible adverse effects of these drugs on neonates, use of TREXIMET in nursing mothers should be avoided.

Pediatric Use

Safety and effectiveness of TREXIMET in pediatric patients have not been established.

Geriatric Use

TREXIMET is contraindicated for use in elderly patients who have abnormal hepatic function, and is not recommended for use in elderly patients who have decreased renal function, higher risk for unrecognized CAD, and increases in blood pressure that may be more pronounced in the elderly (see CONTRAINDICATIONS: Hepatic Impairment, WARNINGS: Cardiovascular Effects, and CLINICAL PHARMACOLOGY: Pharmacokinetics).

ADVERSE REACTIONS

The adverse reactions reported below are specific to the clinical trials with TREXIMET. See also the full prescribing information for naproxen and sumatriptan products.

Incidence in Controlled Clinical Trials

Table 2 lists adverse events that occurred in 2 placebo-controlled clinical trials evaluating patients who took at least 1 dose of study drug. Only events that occurred at a frequency of 2% or more with TREXIMET and were more frequent than in the placebo group are included in Table 2. The events cited reflect experience gained under closely monitored conditions of clinical trials in a highly selected patient population. In actual clinical practice or in other clinical trials, these frequency estimates may not apply, as the conditions of use, reporting behavior, and the kinds of patients treated may differ.

Table 2. Treatment-Emergent Adverse Events Reported by at Least 2% of Patients in 2 Controlled Migraine Trialsa
Adverse Event | Percent of Patients Reporting
Adverse Event | TREXIMET; (n = 737) | Placebo; (n = 752) | Sumatriptan; 85 mg; (n = 735) | Naproxen Sodium; 500 mg; (n = 732)
Nervous system disorders
Dizziness | 4 | 2 | 2 | 2
Somnolence | 3 | 2 | 2 | 2
Paresthesia | 2 | <1 | 2 | <1
Gastrointestinal disorders
Nausea | 3 | 1 | 3 | <1
Dyspepsia | 2 | 1 | 2 | 1
Dry mouth | 2 | 1 | 2 | <1
Pain and other pressure sensations
Chest discomfort/chest pain | 3 | <1 | 2 | 1
Neck/throat/jaw pain/tightness/pressure | 3 | 1 | 3 | 1
aEvents that occurred at a frequency of 2% or more in the group treated with TREXIMET and that occurred more frequently in the group treated with TREXIMET than in the placebo group.

Other events that occurred in more than 1% of patients receiving TREXIMET and occurred at a frequency greater than the placebo group included asthenia, feeling hot, muscle tightness, and palpitations.

TREXIMET was generally well tolerated. Most adverse reactions were mild and transient. The incidence of adverse events in controlled clinical trials was not affected by gender or age of the patients. There were insufficient data to assess the impact of race on the incidence of adverse events.

Other Events Observed in Migraine Clinical Trials Associated With the Administration of TREXIMET

The occurrence of less commonly reported adverse clinical events is presented in this section. Because the reports include events observed in an open-label, long-term safety study in which TREXIMET was used as needed for up to 12 months, the role of TREXIMET cannot be reliably determined. Furthermore, variability associated with adverse event reporting, the terminology used to describe adverse events, etc., limit the value of quantitative frequency estimates provided. Event frequencies are calculated as the number of patients who used TREXIMET and reported an event divided by the total number of patients (N = 3,302) exposed to TREXIMET. Events listed in the previous table and text are not included below. Those events described too generally to be informative or those unlikely to be associated with the use of TREXIMET are excluded. Events are further classified within body system categories and enumerated in order of decreasing frequency using the following definitions: frequent adverse events are those occurring in at least 1/100 patients, infrequent adverse events are those occurring in 1/100 to 1/1,000 patients, and rare adverse events are those occurring in fewer than 1/1,000 patients.

Blood and Lymphatic Disorders: Infrequent was lymphadenopathy. Rare were anemia, ecchymosis, leukopenia.

Cardiac Disorders: Infrequent was tachycardia. Rare were acute coronary syndrome, cardiac flutter, congestive cardiac failure, right ventricular failure, ventricular extrasystoles.

Ear and Labyrinth Disorders: Infrequent were ear pain, tinnitus. Rare were motion sickness, vertigo.

Endocrine, Metabolic, and Nutrition Disorders: Rare were diabetes mellitus, goiter, hypoglycemia, hypothyroidism.

Eye Disorders: Infrequent was conjunctivitis. Rare were cataract, conjunctival hemorrhage, visual disturbance.

Gastrointestinal Disorders: Frequent was abdominal pain. Infrequent were abdominal distention, constipation, diarrhea, dysgeusia, dysphagia, flatulence, gastritis, gastroesophageal reflux disease, vomiting. Rare were colitis, diverticulitis, gastric ulcer, irritable bowel syndrome, oral mucosal blistering, swollen tongue.

General Disorders: Frequent was fatigue. Infrequent were feeling jittery, lethargy, malaise, peripheral edema, pyrexia, temperature intolerance, thirst. Rare was difficulty in walking.

Hepatobiliary Disorders: Rare was biliary colic.

Infections and Infestations: Rare were kidney infection, pneumonia, sepsis, staphylococcal infection, viral myocarditis.

Musculoskeletal and Connective Tissue: Infrequent were arthralgia, back pain, muscular weakness, myalgia, sensation of heaviness.

Nervous System Disorders: Infrequent were burning sensation, disturbance of attention, insomnia, mental impairment, tremor. Rare were aphasia, facial palsy, impairment of psychomotor skills, sedation.

Psychiatric Disorders: Infrequent were anxiety, depression, irritability, nervousness. Rare were disorientation, panic attack.

Renal and Urinary Disorders: Infrequent was nephrolithiasis. Rare was renal insufficiency.

Respiratory, Thoracic, and Mediastinal: Infrequent were asthma, cough, dyspnea, oropharyngeal swelling. Rare was pleurisy.

Skin and Subcutaneous Disorders: Infrequent were facial swelling, hyperhydrosis, pruritus, rash, urticaria. Rare was systemic lupus erythematosus.

Vascular Disorders: Infrequent were flushing, hot flush, hypertension. Rare were epistaxis, peripheral coldness.

DRUG ABUSE AND DEPENDENCE

The potential for abuse with TREXIMET has not been studied.

One clinical study with sumatriptan succinate injection enrolling 12 patients with a history of substance abuse failed to induce subjective behavior and/or physiologic response ordinarily associated with drugs that have an established potential for abuse.

OVERDOSAGE

Because strategies for the management of overdose are continually evolving, it is advisable to contact a Poison Control Center to determine the latest recommendations for the management of an overdose of any drug.

There have been no reports of overdosage with TREXIMET. Since sumatriptan and naproxen have pharmacologically different actions, it is difficult to predict how an individual will respond to an overdosage with TREXIMET.

Patients (N = 670) have received single oral doses of 140 to 300 mg of sumatriptan without significant adverse effects. Volunteers (N = 174) have received single oral doses of 140 to 400 mg without serious adverse events. Overdose of sumatriptan in animals has been fatal and has been heralded by convulsions, tremor, paralysis, inactivity, ptosis, erythema of the extremities, abnormal respiration, cyanosis, ataxia, mydriasis, salivation, and lacrimation.

Significant naproxen overdosage may be characterized by lethargy, dizziness, drowsiness, epigastric pain, abdominal discomfort, heartburn, indigestion, nausea, transient alterations in liver function, hypoprothrombinemia, renal dysfunction, metabolic acidosis, apnea, disorientation, or vomiting. Gastrointestinal bleeding can occur. Hypertension, acute renal failure, respiratory depression, and coma may occur, but are rare. Anaphylactoid reactions have been reported with therapeutic ingestion of NSAIDs, and may occur following an overdose. Because naproxen sodium may be rapidly absorbed, high and early blood levels should be anticipated. A few patients have experienced seizures, but it is not clear whether or not these were drug related. It is not known what dose of the drug would be life threatening.

In animals 0.5 g/kg of activated charcoal was effective in reducing plasma levels of naproxen. Patients should be managed by symptomatic and supportive care. There are no specific antidotes. Hemodialysis does not decrease the plasma concentration of naproxen because of the high degree of its protein binding. It is unknown what effect hemodialysis or peritoneal dialysis has on the serum concentrations of sumatriptan. Emesis and/or activated charcoal (60 to 100 g in adults, 1 to 2 g/kg in children) and/or osmotic cathartic may be indicated in patients seen within 4 hours of ingestion with symptoms or following a large overdose. Forced diuresis, alkalinization of urine, or hemoperfusion may not be useful due to high protein binding.

DOSAGE AND ADMINISTRATION

TREXIMET is a fixed combination containing doses of sumatriptan (85 mg) and naproxen sodium (500 mg) within the approved dosage ranges of the individual components (25 to 100 mg of sumatriptan and 220 to 825 mg of naproxen sodium). TREXIMET contains a dose of sumatriptan higher than the lowest effective dose. Individuals may vary in response to doses of sumatriptan. The choice of the dose of sumatriptan, and of the use of a fixed combination such as in TREXIMET should therefore be made on an individual basis, weighing the possible benefit of a higher dose of sumatriptan with the potential for a greater risk of adverse events. Carefully consider the potential benefits and risks of TREXIMET and other treatment options when deciding to use TREXIMET.

The recommended dose is 1 tablet. In controlled clinical trials, single doses of TREXIMET were effective for the acute treatment of migraine in adults (see CLINICAL TRIALS).

The efficacy of taking a second dose has not been established. Do not take more than 2 TREXIMET tablets in 24 hours. Dosing of tablets should be at least 2 hours apart. The safety of treating an average of more than 5 migraine headaches in a 30-day period has not been established.

TREXIMET may be administered with or without food. Tablets should not be split, crushed, or chewed.

The combined use of TREXIMET with MAO-A inhibitors or use of TREXIMET within 2 weeks of discontinuation of MAO-A inhibitor therapy is contraindicated (see CONTRAINDICATIONS, CLINICAL PHARMACOLOGY: Drug Interactions, PRECAUTIONS: Drug Interactions).

TREXIMET and any ergotamine-containing or ergot-type medication (like dihydroergotamine or methysergide) should not be used within 24 hours of each other. TREXIMET and other 5-HT1 agonists should not be administered within 24 hours of each other (see CONTRAINDICATIONS and PRECAUTIONS: Drug Interactions).

TREXIMET is contraindicated in patients with hepatic impairment (see CONTRAINDICATIONS and CLINICAL PHARMACOLOGY: Special Populations).

TREXIMET is not recommended for use in patients with creatinine clearance less than 30 mL/min (see CLINICAL PHARMACOLOGY: Special Populations and PRECAUTIONS: Renal Effects).

HOW SUPPLIED

TREXIMET contains 119 mg of sumatriptan succinate equivalent to 85 mg of sumatriptan and 500 mg of naproxen sodium and is supplied as blue film-coated tablets debossed on one side with TREXIMET in compact containers of 9 tablets with a specially formulated, non-removable desiccant (NDC 21695-954-09).

Store at 25°C (77°F); excursions permitted to 15°-30°C (59°-86°F) [see USP Controlled Room Temperature]. Do not repackage; dispense and store in original container.

ANIMAL TOXICOLOGY

Corneal Opacities

Dogs receiving oral sumatriptan developed corneal opacities and defects in the corneal epithelium. Corneal opacities were seen at the lowest dosage tested, 2 mg/kg/day, and were present after 1 month of treatment. Defects in the corneal epithelium were noted in a 60-week study. Earlier examinations for these toxicities were not conducted and no-effect doses were not established; the lowest dose tested is approximately 0.8 times the recommended human oral daily dose of 85 mg sumatriptan on a mg/m^2 basis. There was evidence of alterations in corneal appearance on the first day of intranasal dosing to dogs at all doses tested.

MEDICATION GUIDE

TREXIMET® [trex' i-met] Tablets

(sumatriptan and naproxen sodium)

What is the most important information I should know about TREXIMET?

TREXIMET, which contains sumatriptan and naproxen sodium [a nonsteroidal anti-inflammatory drug (NSAID)], may increase the chance of a heart attack or stroke that can lead to death. This chance increases:

- with longer use of NSAID medicines
- in people who have heart disease.

NSAID-containing medicines, such as TREXIMET, should never be used right before or after a heart surgery called a coronary artery bypass graft (CABG).

NSAID-containing medicines, such as TREXIMET, can cause ulcers and bleeding in the stomach and intestines at any time during treatment. Ulcers and bleeding:

- can happen without warning symptoms
- may cause death.

The chance of a person getting an ulcer or bleeding increases with:

- the use of medicines called steroid hormones (corticosteroids) and blood thinners (anticoagulants)
- longer use
- more frequent use
- smoking
- drinking alcohol
- older age
- having poor health.

TREXIMET is not recommended for people with risk factors for heart disease unless a heart exam is done and shows no problems.

The risk factors for heart disease include:

- high blood pressure
- high cholesterol levels
- smoking
- obesity
- diabetes
- family history of heart disease
- female who has gone through menopause
- male over age 40.

“Serotonin syndrome” is a serious and life-threatening problem that may occur with TREXIMET, especially if used with antidepressant medicines called selective serotonin reuptake inhibitors (SSRIs) or selective norepinephrine reuptake inhibitors (SNRIs).

Commonly used SSRIs are:

- CELEXA® (citalopram HBr)
- LEXAPRO® (escitalopram oxalate)
- PAXIL® (paroxetine)
- PROZAC®/SARAFEM® (fluoxetine)
- SYMBYAX® (olanzapine/fluoxetine)
- ZOLOFT® (sertraline)
- LUVOX® (fluvoxamine).

Commonly used SNRIs are:

- CYMBALTA® (duloxetine)
- EFFEXOR® (venlafaxine).

Call your healthcare provider if you have symptoms of serotonin syndrome, which include:

- mental changes (hallucinations, agitation, coma)
- fast heartbeat
- changes in blood pressure
- high body temperature or sweating
- tight muscles
- trouble walking
- nausea, vomiting, diarrhea.

TREXIMET should only be used:

- exactly as prescribed
- at the lowest dose possible for your treatment
- for the shortest time needed.

TREXIMET already contains an NSAID (naproxen). Do not use TREXIMET with other medicines to lessen pain or fever without talking to your healthcare provider first, because they may contain an NSAID also.

What is TREXIMET?

TREXIMET is a prescription medicine used to treat migraine attacks in adults. It does not prevent or lessen the number of migraines you have, and it is not for other types of headaches. TREXIMET contains 2 medicines: sumatriptan and naproxen sodium (an NSAID). This Medication Guide provides important information you need to know before taking TREXIMET. It does not take the place of talking with your healthcare provider about your medical condition or your treatment.

How should I take TREXIMET?

- Take 1 TREXIMET tablet to treat your migraine headache. Do not take more than 2 TREXIMET tablets in 24 hours. Doses should be separated by at least 2 hours.
- TREXIMET can be taken with or without food.
- Do not split, crush, or chew TREXIMET tablets.
- If you take too much TREXIMET, call the Poison Control Center at 1-800-222-1222.

Who should not take TREXIMET?

Do not take TREXIMET right before or after heart bypass surgery.

Do not take TREXIMET if you have or have had:

- uncontrolled high blood pressure
- hemiplegic or basilar migraine. (Ask your doctor if you are not sure what type of migraine you have.)
- liver problems
- an asthma attack, hives, or other allergic reaction with aspirin or any other NSAID medicine
- a heart attack or a history or symptoms of heart disease (such as chest pain or angina)
- a stroke, mini-stroke (transient ischemic attack or TIA), or other stroke-like syndrome
- problems with blood circulation to parts of your body, such as less blood flow to your intestines (ischemic bowel disease)
- allergic reactions to sumatriptan, naproxen, or other ingredients in TREXIMET.

Do not take TREXIMET if you take or have taken an antidepressant medicine called a monoamine oxidase (MAO) inhibitor within the last 2 weeks. Common MAO inhibitors are isocarboxazid (MARPLAN®), phenelzine (NARDIL®), tranylcypromine (PARNATE®), and selegiline (ELDEPRYL®, EMSAM®). Ask your healthcare provider if you are not sure if your medicine is an MAO inhibitor.

Do not take TREXIMET if you have taken other migraine medicines in the last 24 hours such as:

- ergotamine-containing medicine or
- another triptan medicine.

Before starting TREXIMET, tell your healthcare provider about:

- all of your medical conditions including kidney or liver problems
- all allergies to any medicines
- chest pain, shortness of breath, irregular heartbeats
- medicines you may take for migraines, depression, or other health problems such as MAO inhibitors, SSRIs, or SNRIs
- all the prescription and non-prescription medicines you take, including vitamins and herbal supplements. Some medicines can interact with TREXIMET and cause serious side effects.

Keep a list of your medicines to show to your healthcare provider.

Before starting TREXIMET, tell your healthcare provider if you:

- are pregnant, think you might be pregnant, or are trying to become pregnant. TREXIMET should not be used by pregnant women late in their pregnancy.
- are breastfeeding
- have a headache that is different from your usual migraine
- have or have had epilepsy or seizures.

What are the possible side effects of TREXIMET?

Serious side effects include:

- heart attack
- heartbeat problems
- stroke
- high blood pressure
- heart failure from body swelling (fluid retention)
- kidney problems including kidney failure
- bleeding and ulcers in the stomach and intestine
- low red blood cells (anemia)
- life-threatening skin reactions
- life-threatening allergic reactions
- liver problems including liver failure
- asthma attacks in people who have asthma
- loss of blood circulation to areas of your body
- serotonin syndrome (See list of symptoms in “What is the most important information I should know about TREXIMET?”)

Other side effects include:

- pain, tightness, or pressure in the chest, neck, and throat
- stomach pain
- constipation
- diarrhea
- gas
- heartburn
- nausea
- vomiting
- dizziness
- drowsiness
- tiredness
- weakness
- tingling and numbness
- unusual body sensations
- redness of face (flushed)

Get emergency help right away if you have any of the following symptoms:

- shortness of breath or trouble breathing
- chest pain
- swelling of the face or throat
- weakness in one part or on one side of your body
- slurred speech.

Stop TREXIMET and call your healthcare provider right away if you have any of the following symptoms:

- nausea that seems out of proportion to your migraine
- stomach pain
- sudden/severe pain in your belly
- vomit blood
- blood in your bowel movement or it is black and sticky like tar
- itching
- skin rash or blisters with fever
- yellow skin or eyes
- swelling of the arms and legs, hands, feet, face, lips, or tongue
- unusual weight gain
- more tired or weaker than usual
- flu-like symptoms
- serotonin syndrome. See list of symptoms in “What is the most important information I should know about TREXIMET?”

Tell your healthcare provider if you have any side effects that bother you or do not go away. These are not all of the side effects of TREXIMET. For more information ask your healthcare provider.

Call your healthcare provider for medical advice about side effects. You may report side effects at FDA at 1-800-FDA-1088.

How should I store TREXIMET?

- Store TREXIMET at room temperature, 59° to 86°F (15° to 30°C).
- Keep TREXIMET and all medicines out of the reach of children.

General information about TREXIMET

- Medicines are sometimes prescribed for purposes other than those listed in a Medication Guide. Do not use TREXIMET for a condition for which it was not prescribed.
- Do not give TREXIMET to other people, even if they have the same problem you have. It may harm them.
- This Medication Guide contains the most important information about TREXIMET. If you would like more information, talk with your healthcare provider.
- You can ask your healthcare provider for information written for healthcare professionals.
- For more information call 1-888-825-5249 (toll-free), or visit www.TREXIMET.com.

What are the ingredients in TREXIMET?

Active ingredients: sumatriptan succinate and naproxen sodium

Inactive ingredients: croscarmellose sodium, dextrose monohydrate, dibasic calcium phosphate, FD&C Blue No. 2, lecithin, magnesium stearate, maltodextrin, microcrystalline cellulose, povidone, sodium bicarbonate, sodium carboxymethylcellulose, talc, and titanium dioxide.

This Medication Guide has been approved by the U.S. Food and Drug Administration.

June 2009 TRX:3MG

TREXIMET is a trademark of GlaxoSmithKline. IMITREX, PARNATE, and PAXIL are registered trademarks of GlaxoSmithKline.

The other brands listed are trademarks of their respective owners and are not trademarks of GlaxoSmithKline. The makers of these brands are not affiliated with and do not endorse GlaxoSmithKline or its products.

GlaxoSmithKline

Research Triangle Park, NC 27709

©2009, GlaxoSmithKline. All rights reserved.

December 2009 TRX:5PI

Repackaged by:

Rebel Distributors Corp

Thousand Oaks, CA 91320